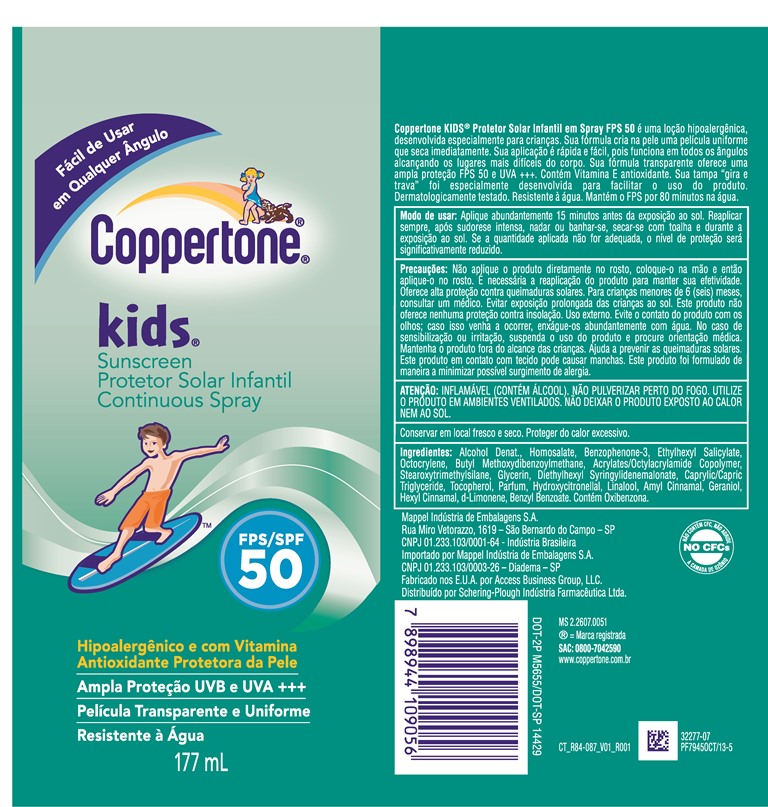 DRUG LABEL: Coppertone

NDC: 11523-7384 | Form: SPRAY
Manufacturer: Bayer HealthCare LLC.
Category: otc | Type: HUMAN OTC DRUG LABEL
Date: 20200120

ACTIVE INGREDIENTS: AVOBENZONE 25.76 mg/1 mL; HOMOSALATE 85.87 mg/1 mL; OCTOCRYLENE 34.34 mg/1 mL; OCTISALATE 39.07 mg/1 mL; OXYBENZONE 42.94 mg/1 mL
INACTIVE INGREDIENTS: ALCOHOL; STEAROXYTRIMETHYLSILANE; GLYCERIN; TOCOPHEROL; MEDIUM-CHAIN TRIGLYCERIDES

Coppertone Kids Continuous Spray SPF 50

ACTIVE INGREDIENT

Each 1mL contains:

Avobenzone 25.76mg

Homosalate 85.87mg

Octisalate 39.07mg

Octocrylene 34.34mg

Oxybenzone 42.94mg